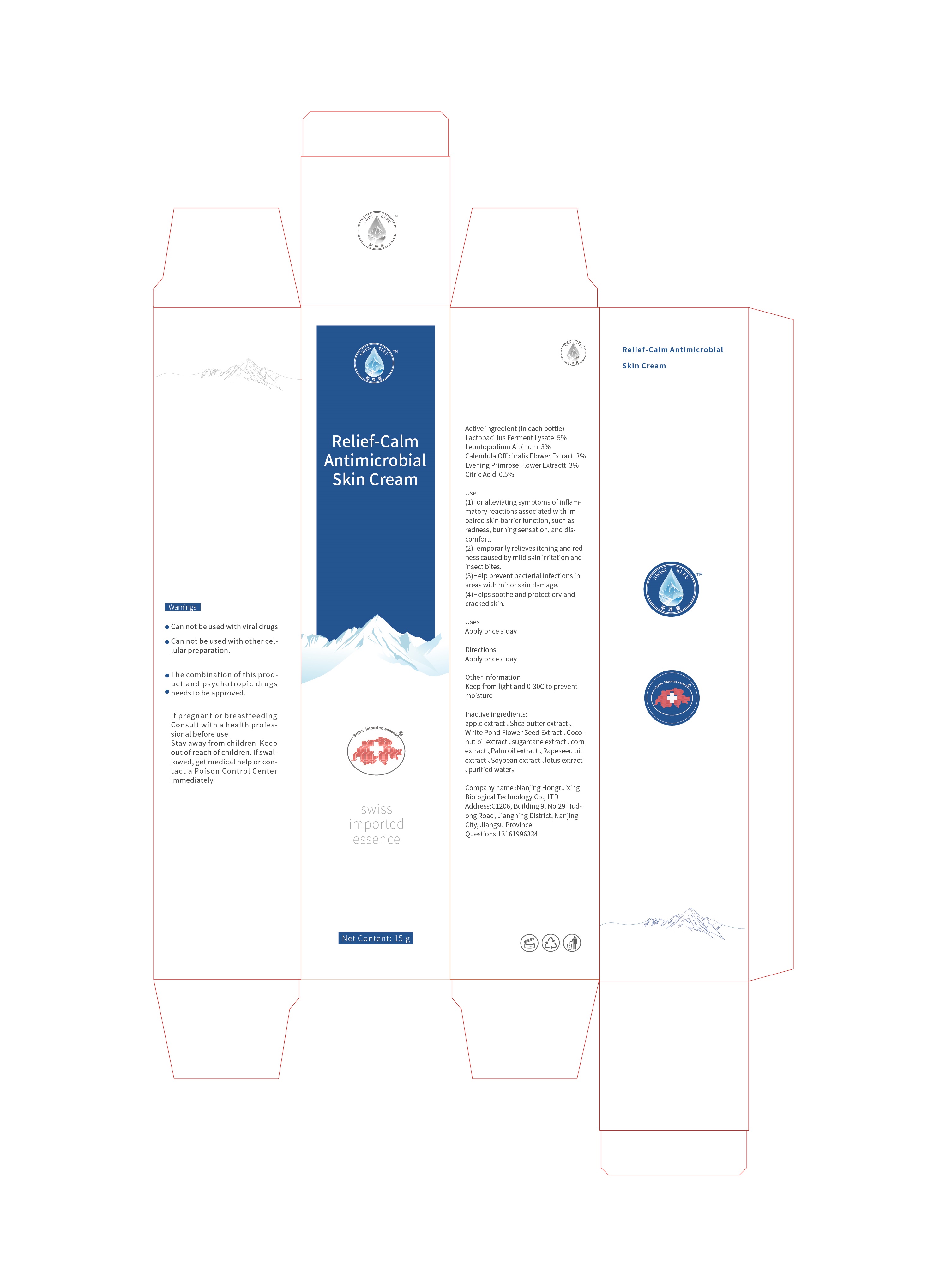 DRUG LABEL: SWISS BLEU Relief-Calm Antimicrobial Skin Cream
NDC: 87321-001 | Form: CREAM
Manufacturer: Nanjing Hongruixing Biological Technology Co., Ltd
Category: otc | Type: HUMAN OTC DRUG LABEL
Date: 20260116

ACTIVE INGREDIENTS: CALENDULA OFFICINALIS FLOWER 3 g/100 g; CITRIC ACID 5 g/100 g; OENOTHERA BIENNIS FLOWER 3 g/100 g; LEONTOPODIUM ALPINUM 3 g/100 g; LACTOBACILLUS ACIDOPHILUS 5 g/100 g
INACTIVE INGREDIENTS: COCONUT OIL; SUGARCANE; PYRUS MALUS (APPLE) FRUIT; SOYBEAN; BRASSICA NAPUS SEED OIL; WATER; SHEANUT OIL; CORN; PALM OIL; NELUMBO NUCIFERA WHOLE; MEADOWFOAM SEED OIL

87321-001

Active ingredients（in each bottle）

Lactobacillus Ferment Lysate 5%

Leontopodium Alpinum 3%

Calendula Officinalis Flower Extract 30%

Evening Primrose Flower Extractt 30%

Citric Acid 0.5%

Purpose

Antimicrobial

Uses

1,For alleviating symptoms of inflammatory reactions associated with impaired skin barrier function, such as redness, burning sensation, and discomfort

2,Temporarily relieves itching and redness caused by mild skin irritation and insect bites

3,Help prevent bacterial infections in areas with minor skin damage

4,Helps soothe and protect dry and cracked skin

Warnings

Can not be used with viral drugs.

Can not be used with other cellular preparation.

The combination of this product and psychotropic drugs needs to be approved.

Keep out of reach of children

Keep out of reach of children

Directions

Apply once a day

Inactive ingredients

Apple extract, Shea butter extract, White Pond Flower Seed Extract, Coconut oil extract, sugarcane extract, corn extract, Palm oil extract, Rapeseed oil extract , Soybean extract, lotus extract, purified water